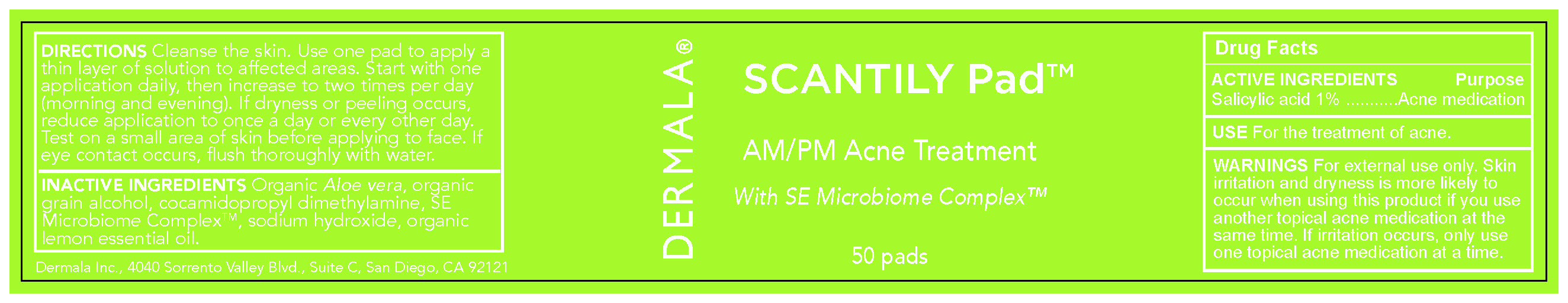 DRUG LABEL: SCANTILY PAD
NDC: 81953-100 | Form: LIQUID
Manufacturer: Dermala Inc
Category: otc | Type: HUMAN OTC DRUG LABEL
Date: 20260119

ACTIVE INGREDIENTS: SALICYLIC ACID 0.01 mg/1 mg
INACTIVE INGREDIENTS: WATER 0.8 mg/1 mg

ACTIVE INGREDIENT

Salicylic acid 1% ...........Acne Treatment

PURPOSE

For the treatment of ACNE

WARNINGS For external use only. Skin
irritation and dryness is more likely to
occur when using this product if you use
another topical acne medication at the
same time. If irritation occurs, only use
one topical acne medication at a time.

INDICATIONS AND USAGE

For the treatment of Acne

INACTIVE INGREDIENTS Organic Aloe vera, organic
grain alcohol, cocamidopropyl dimethylamine, SE
Microbiome ComplexTM, sodium hydroxide, organic
lemon essential oil.

DOSAGE AND ADMINISTRATION

DIRECTIONS Cleanse the skin. Use one pad to apply a
thin layer of solution to affected areas. Start with one
application daily, then increase to two times per day
(morning and evening). If dryness or peeling occurs,
reduce application to once a day or every other day.
Test on a small area of skin before applying to face. If
eye contact occurs, flush thoroughly with water.

Keep out of reach of children